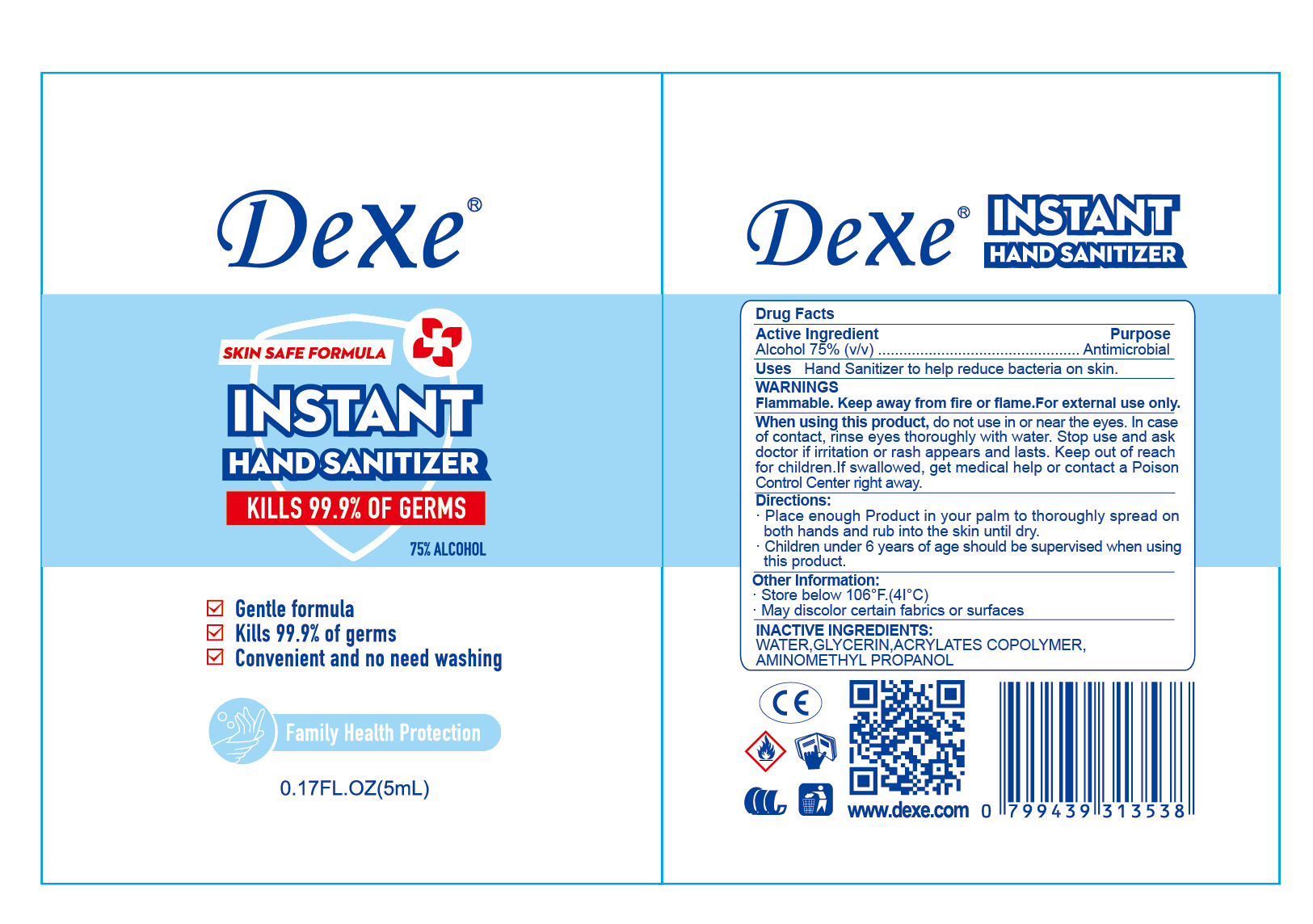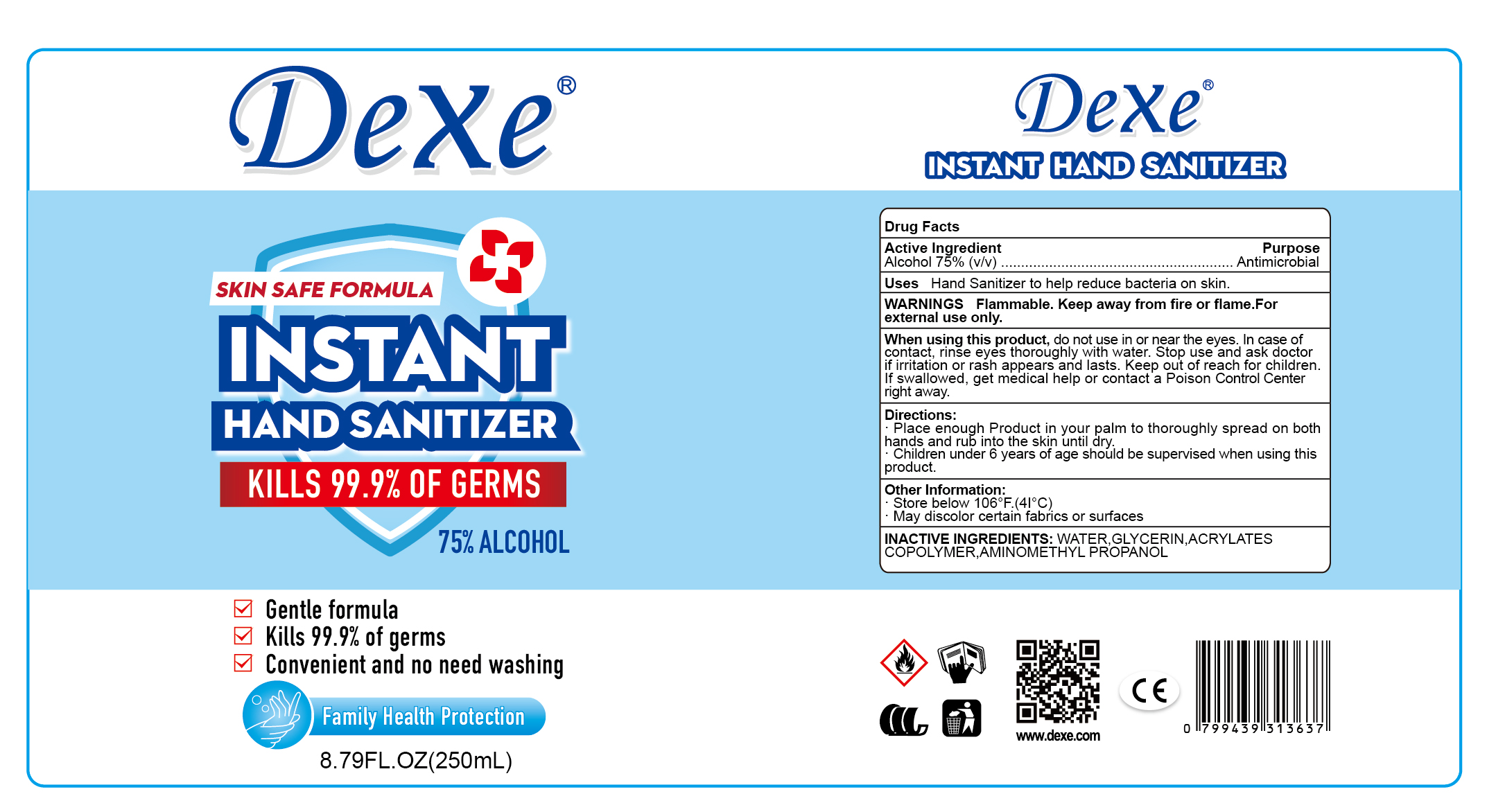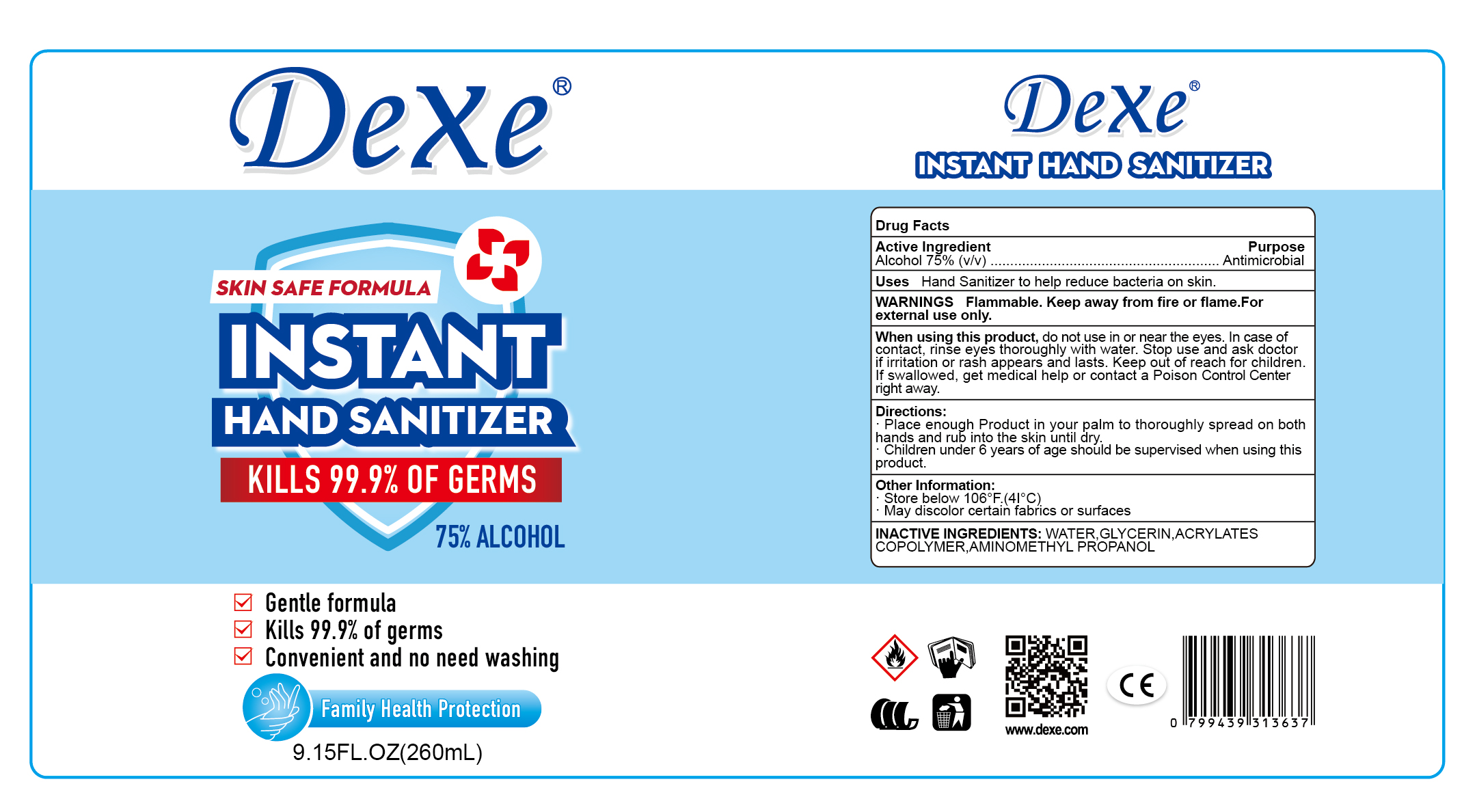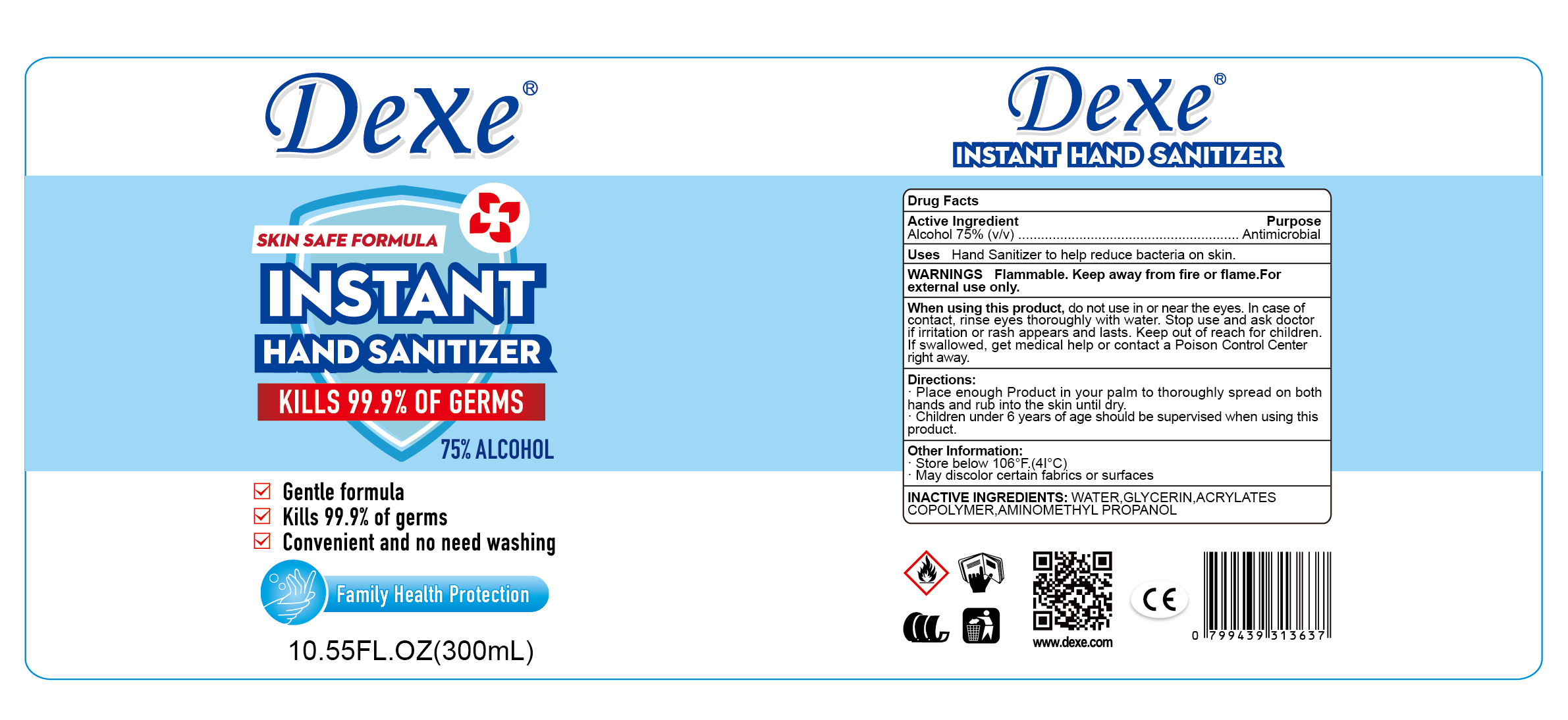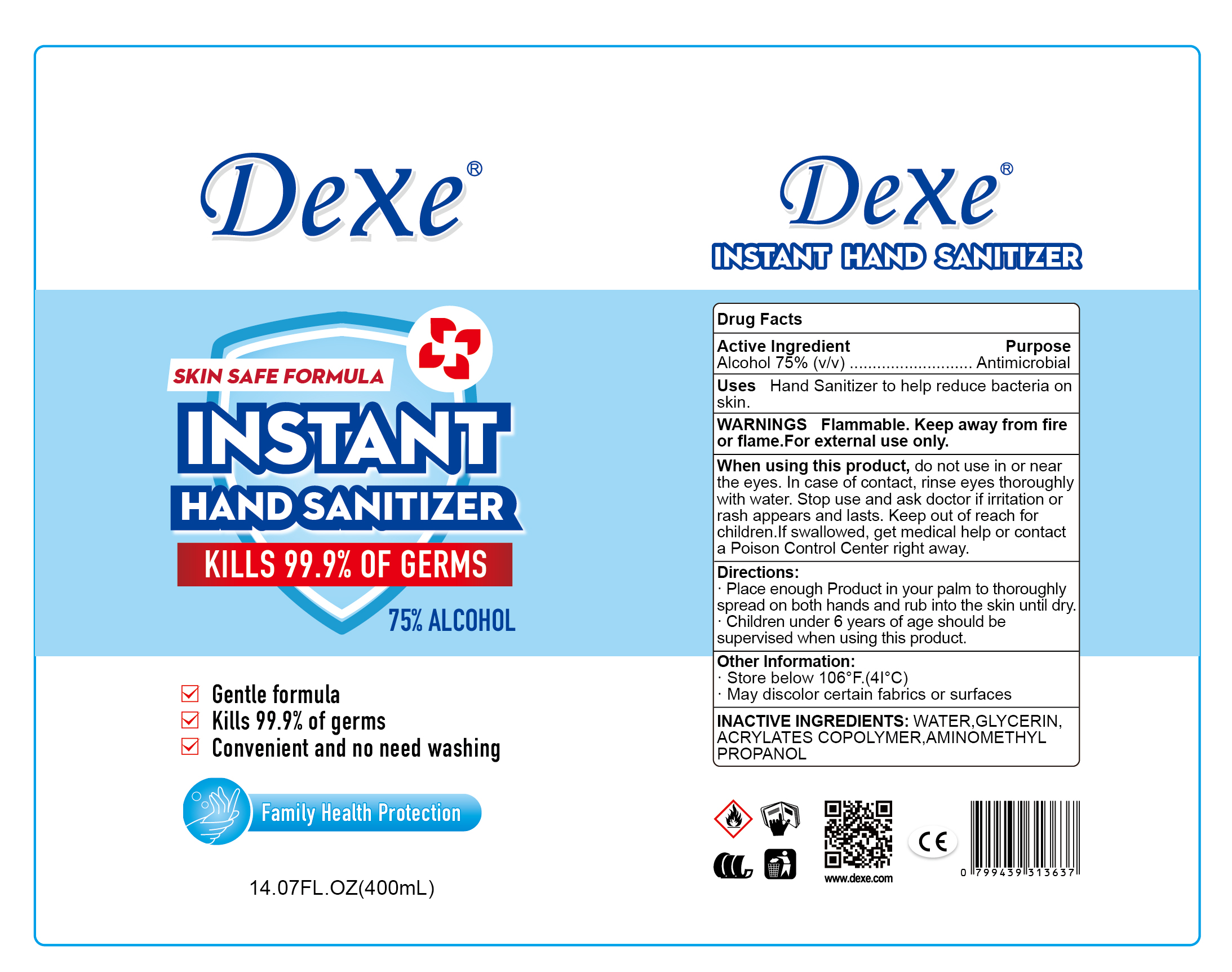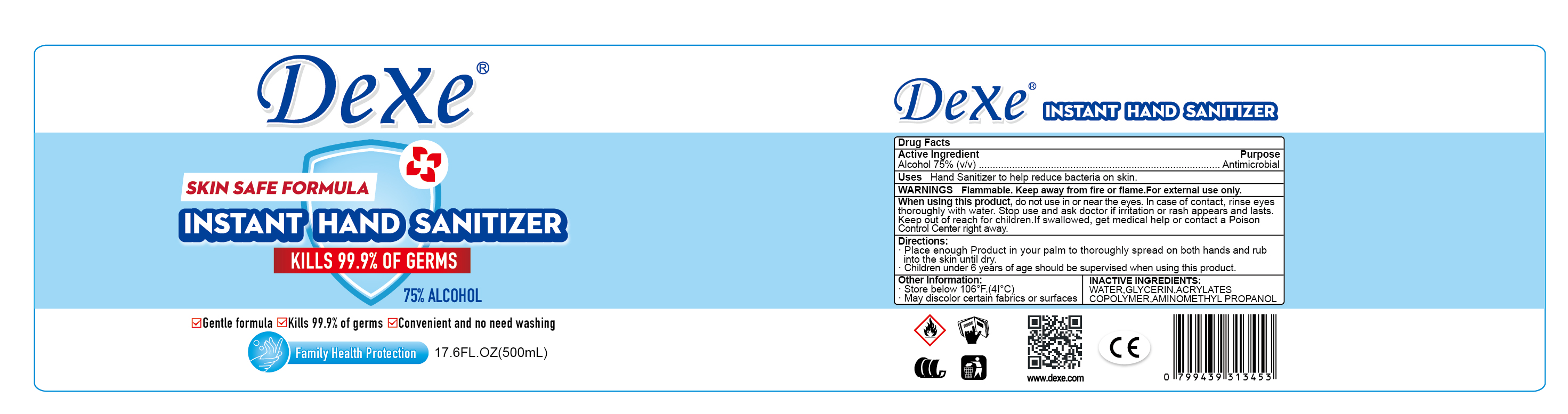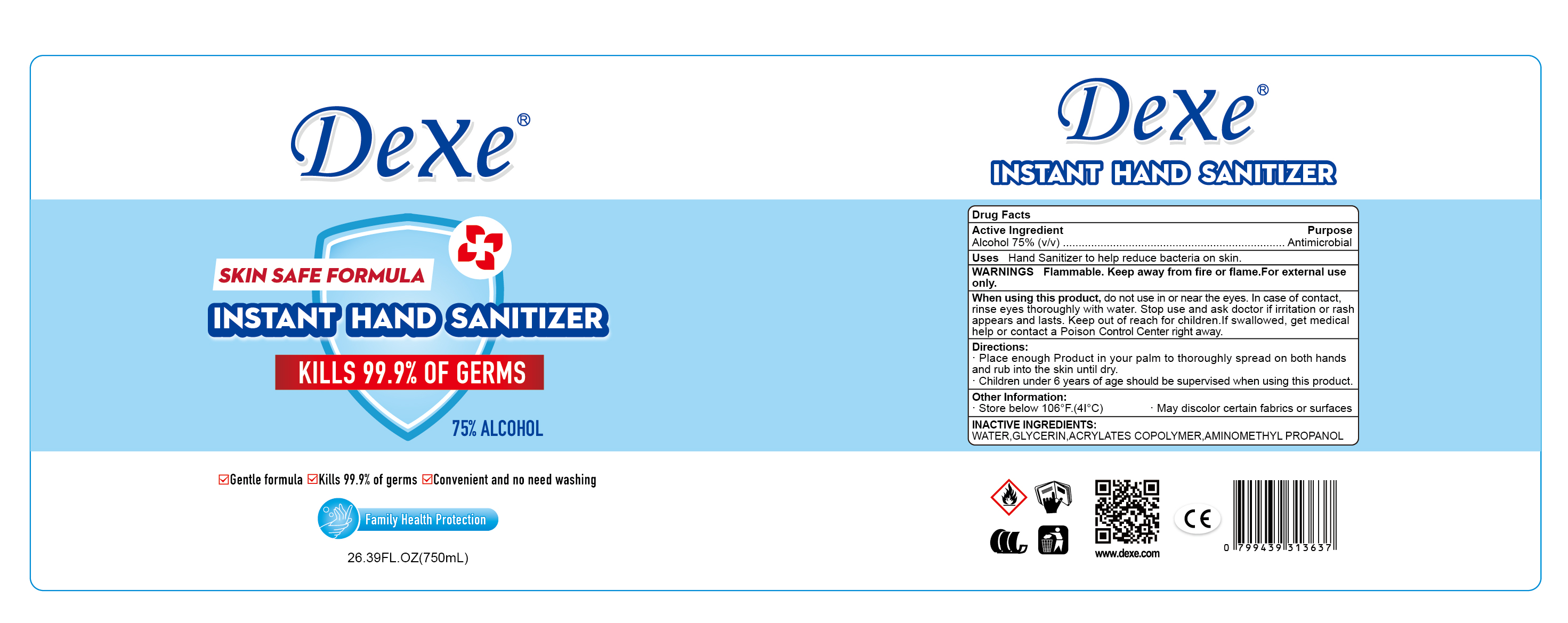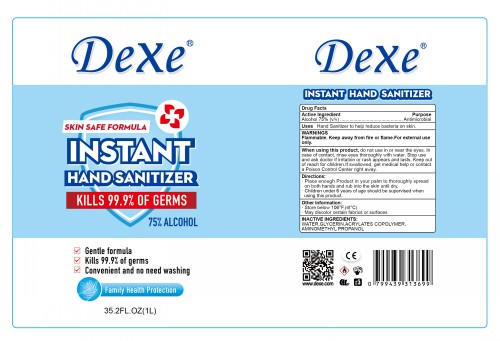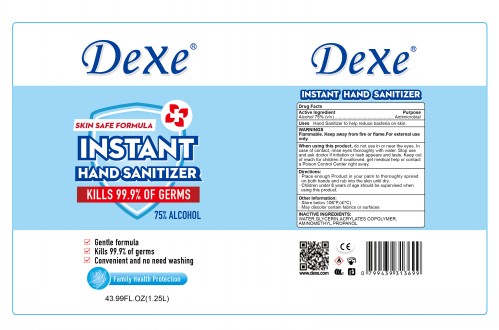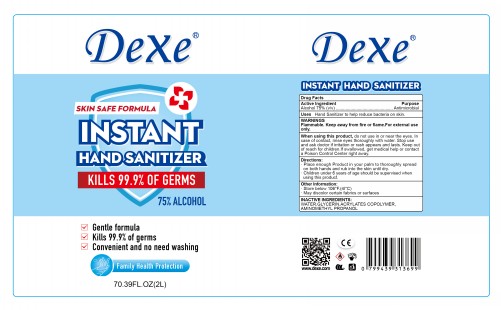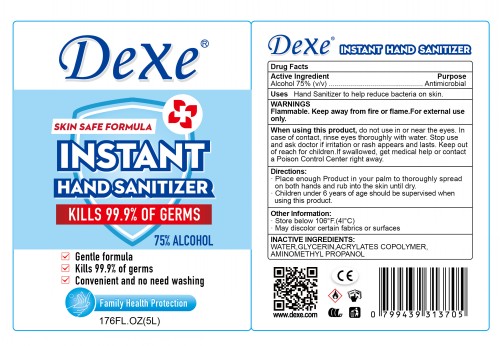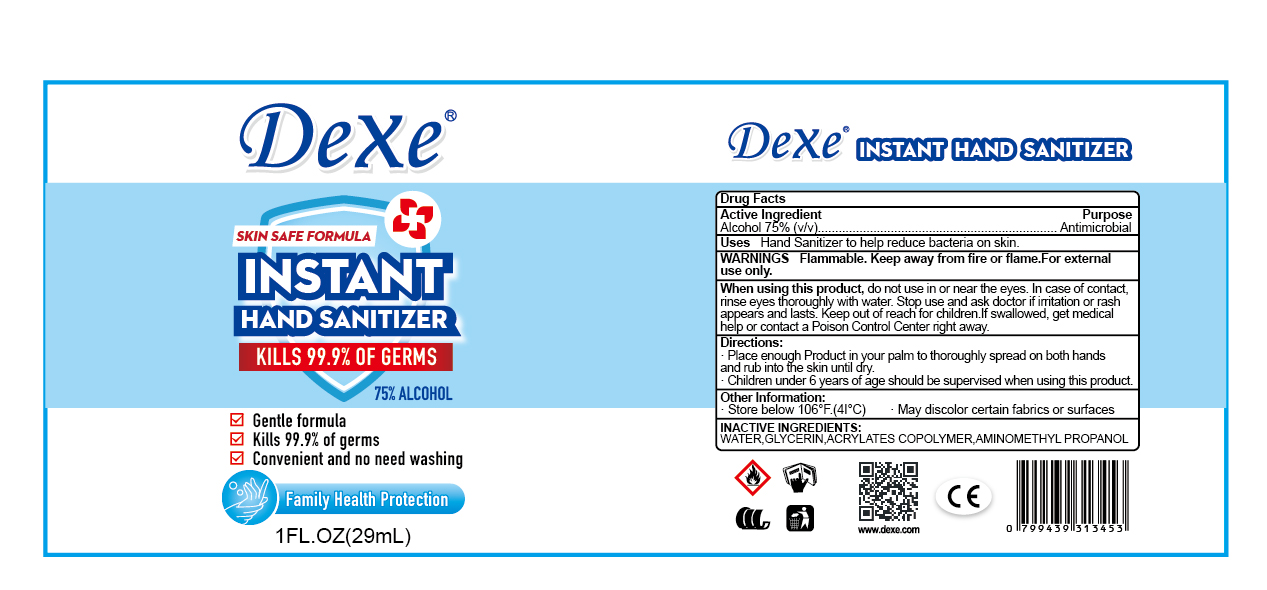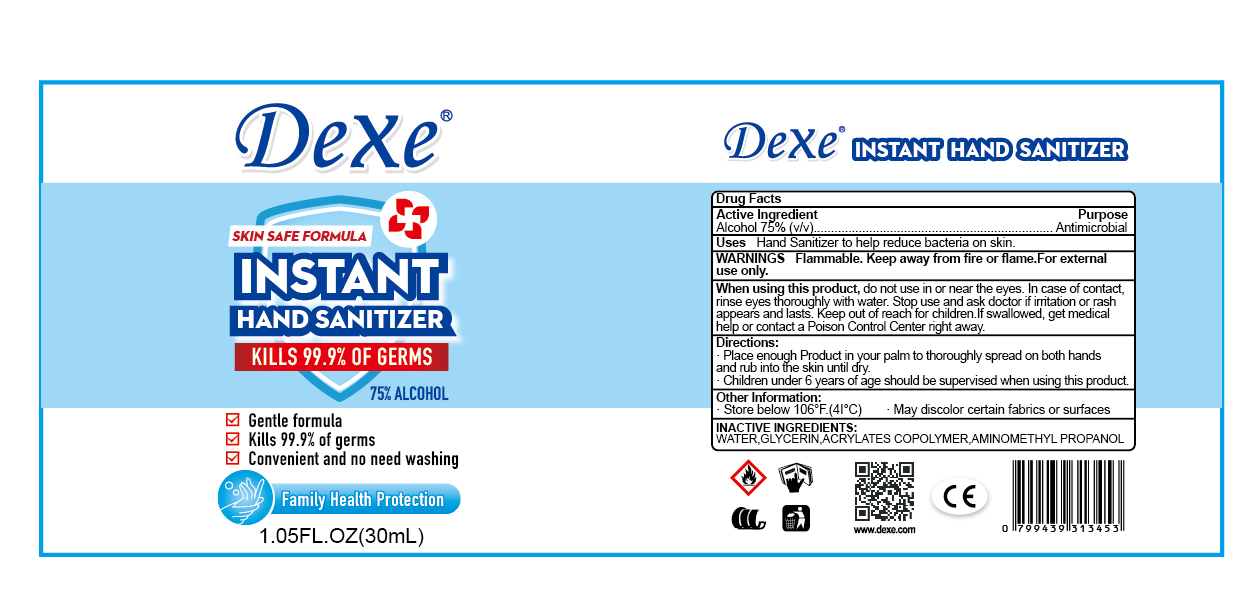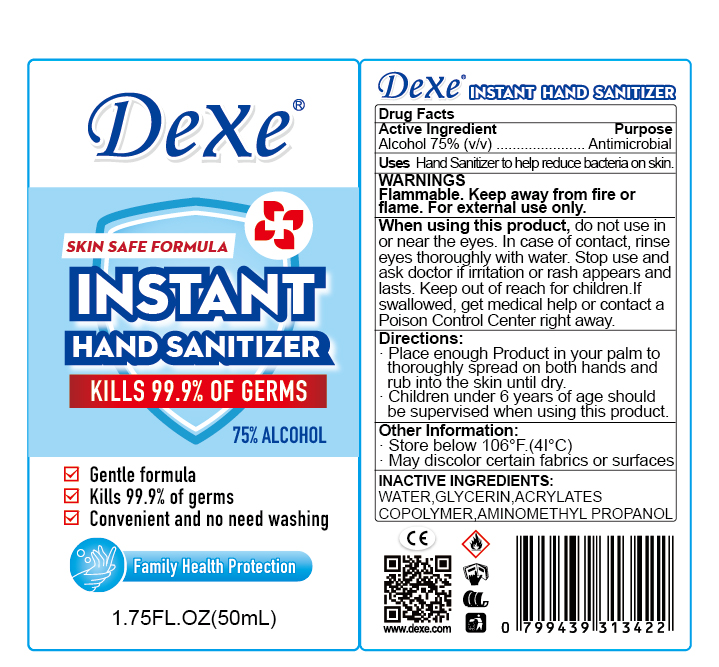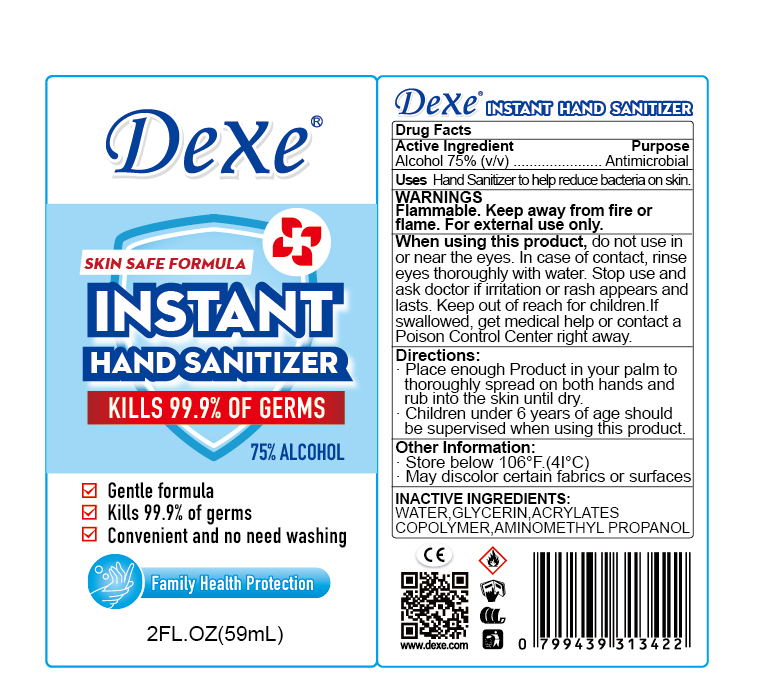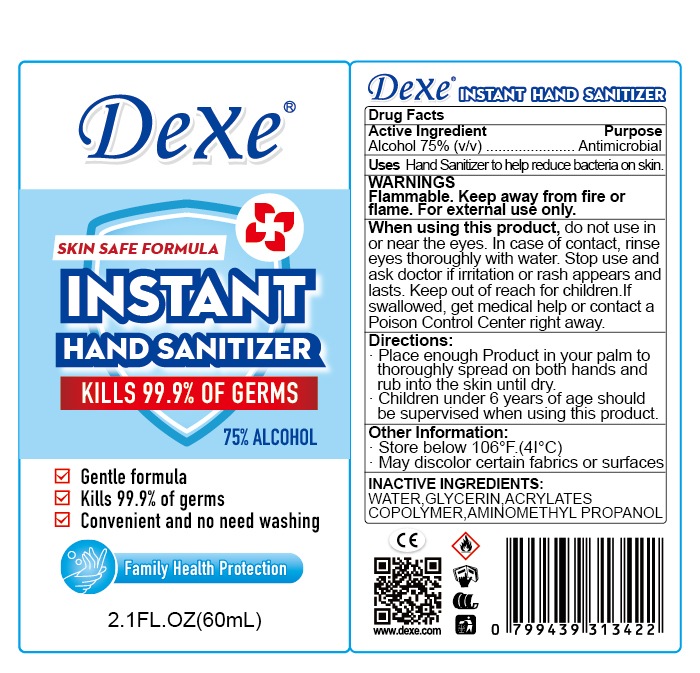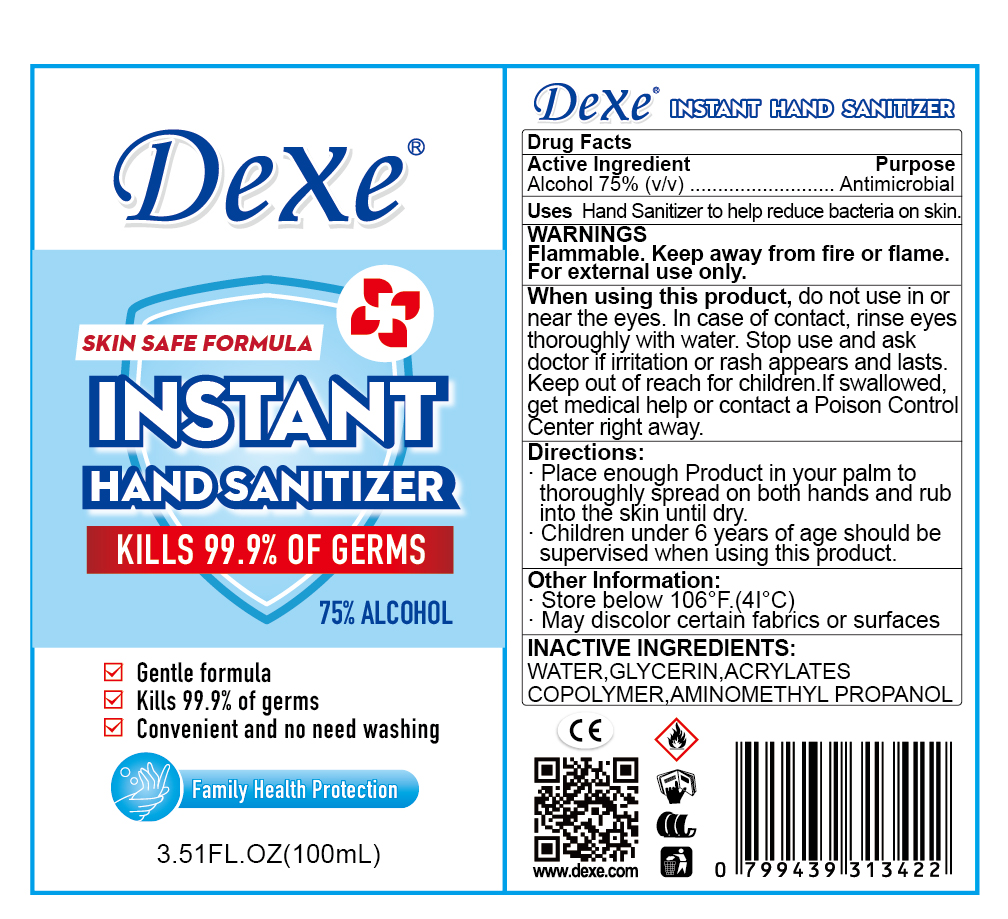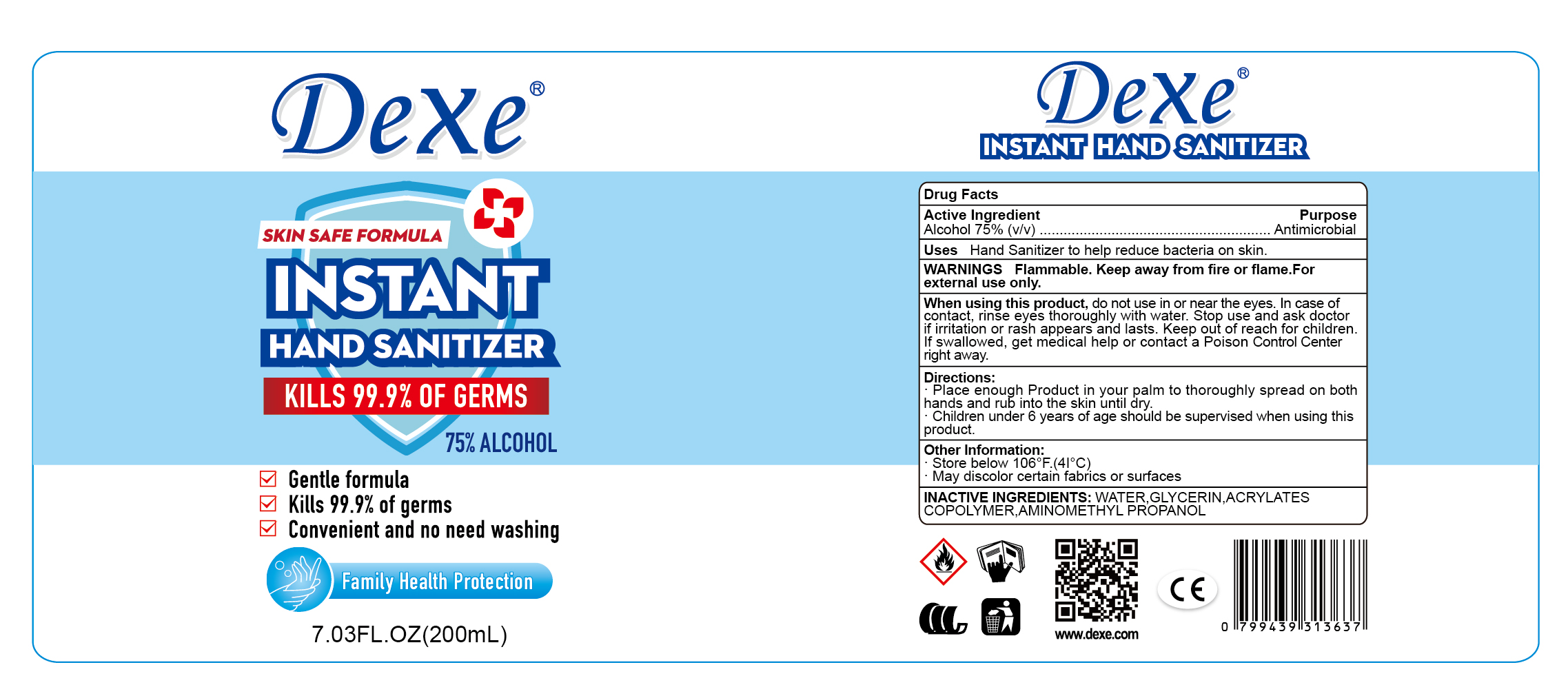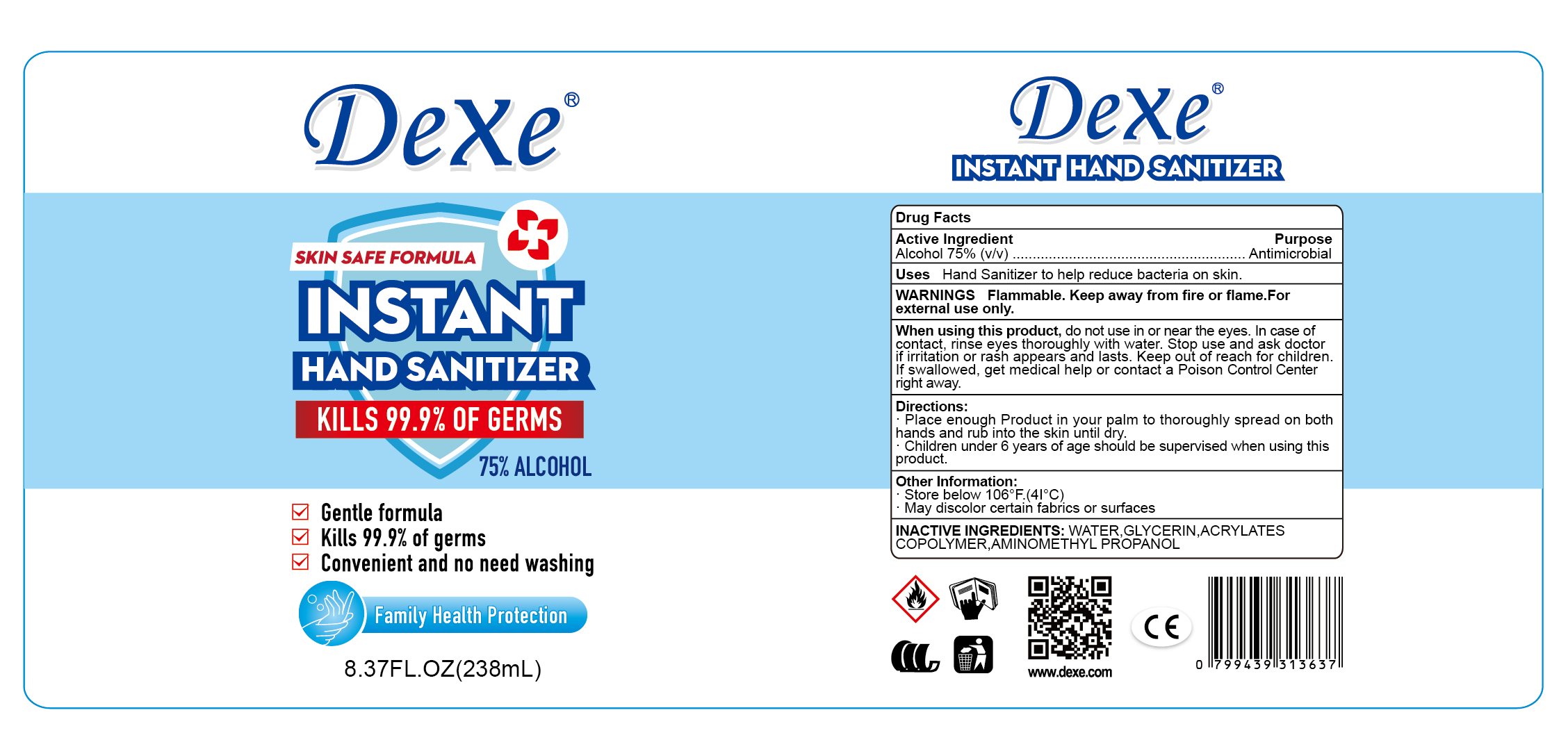 DRUG LABEL: Instant Hand Sanitizer
NDC: 75439-003 | Form: GEL
Manufacturer: Guangzhou Yucaitang Cosmetics Co., Ltd.
Category: otc | Type: HUMAN OTC DRUG LABEL
Date: 20200515

ACTIVE INGREDIENTS: ALCOHOL 75 mL/100 mL
INACTIVE INGREDIENTS: BUTYL ACRYLATE/METHYL METHACRYLATE/METHACRYLIC ACID COPOLYMER (18000 MW); WATER; GLYCERIN; AMINOMETHYLPROPANOL

Instant Hand Sanitizer

Active Ingredient

Alcohol 75%(v/v)

Purpose

Antimicrobial

Uses

Hand Sanitizer to help reduce bacteria on skin.

WARNINGS

Flammable.Keep away from fire or flame.For external use only.

When using this product

do not use in or near the eyes.In case of contact,rinse eyes thoroughly with water.Stop use and ask doctor if irritation or rash appears and lasts.Keep out of reach for children.lf swallowed,get medical help or contact a Poison Control Center right away.

Directions

Place enough Product in your palm to thoroughly spread on

both hands and rub into the skin until dry.

Children under 6 years of age should be supervised when using

this product.

Other Information

Store below 106°F.(4I°C)

May discolor certain fabrics or surfaces

INACTIVE INGREDIENTS

WATER,GLYCERIN, ACRYLATES COPOLYMER,AMINOMETHYL PROPANOL